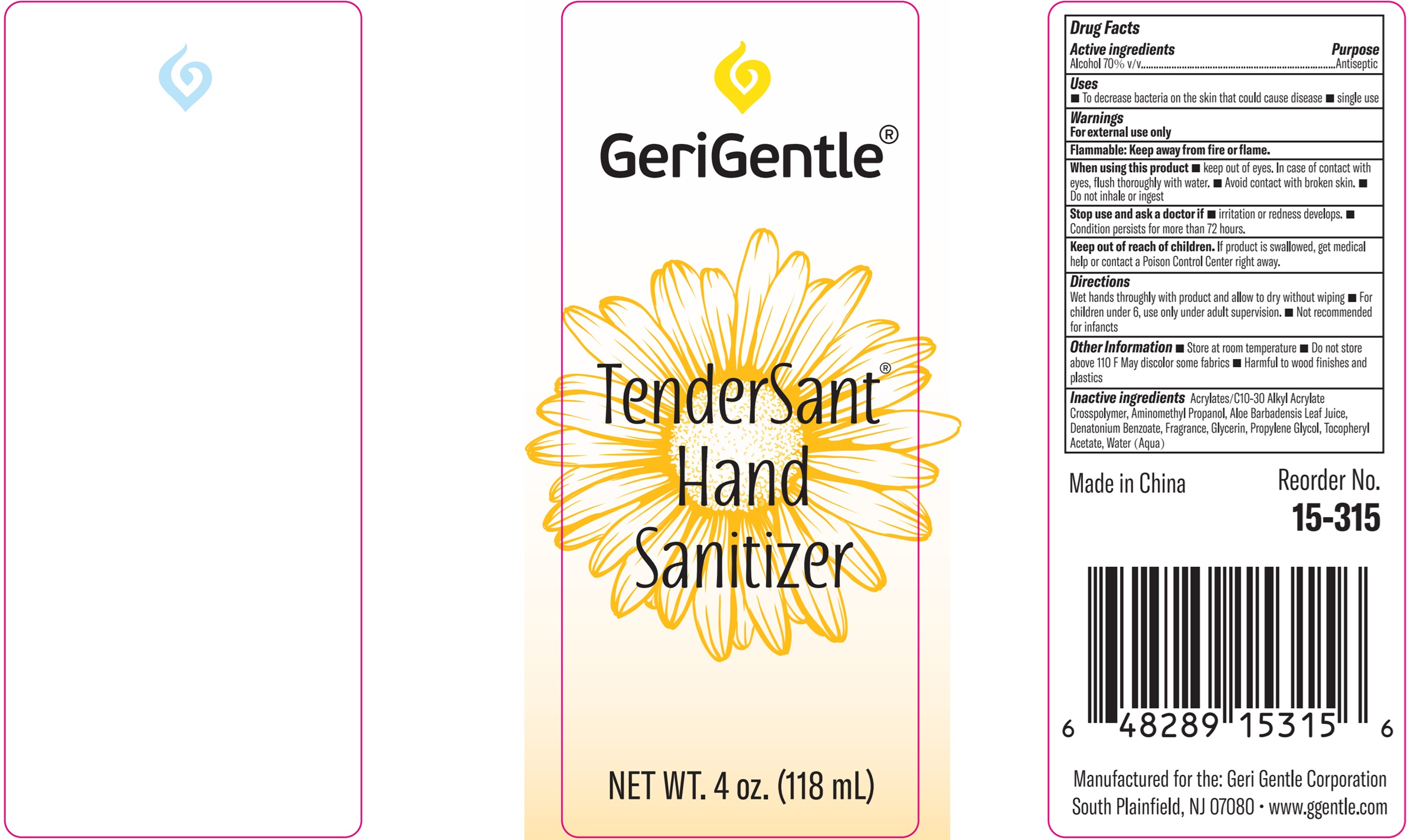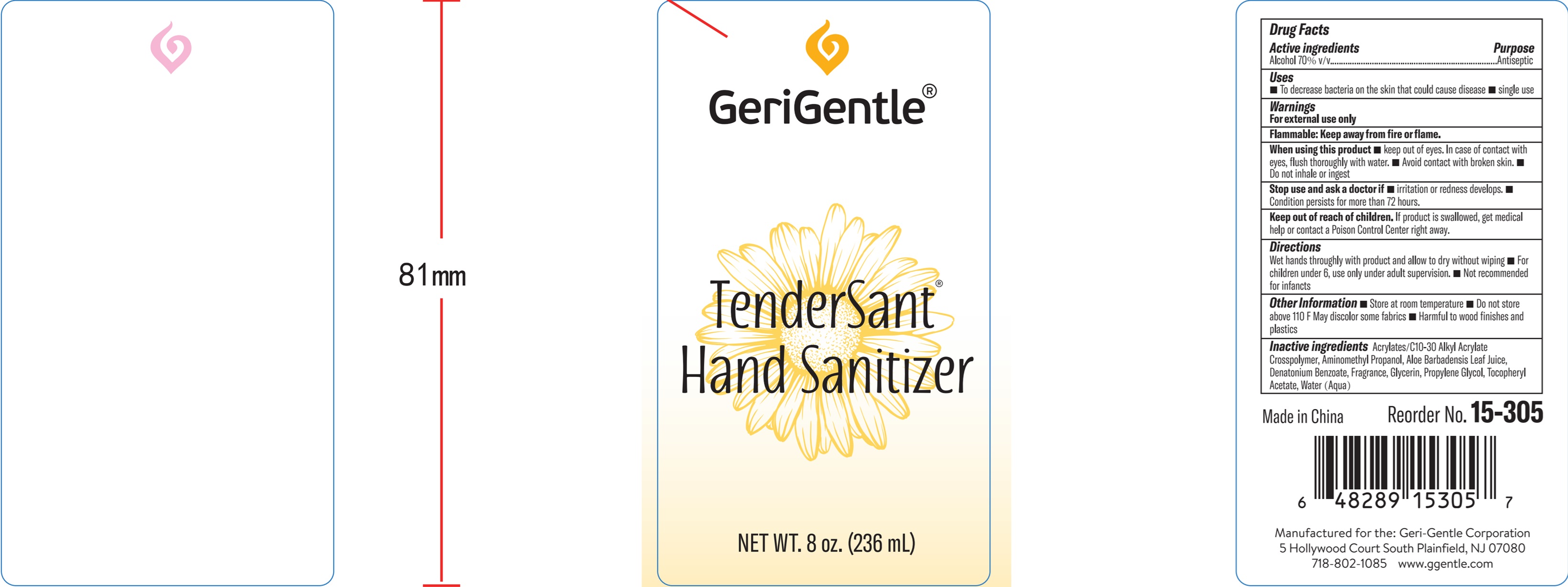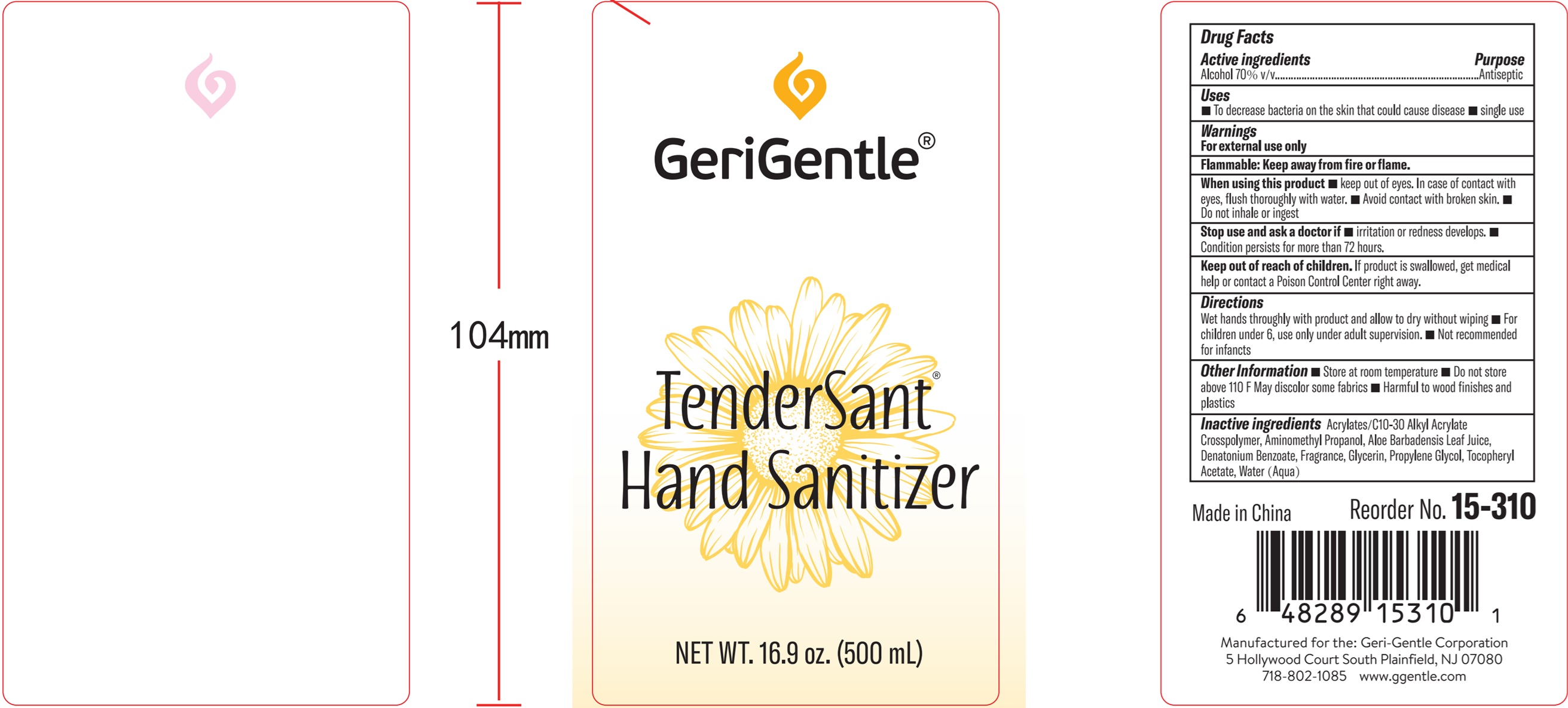 DRUG LABEL: Tendersant Hand Sanitizer
NDC: 69771-007 | Form: GEL
Manufacturer: Geri-Gentle Corporation
Category: otc | Type: HUMAN OTC DRUG LABEL
Date: 20250923

ACTIVE INGREDIENTS: ALCOHOL 0.7 mL/1 mL
INACTIVE INGREDIENTS: WATER; ALOE VERA LEAF; MALTODEXTRIN; GLYCERIN; PROPYLENE GLYCOL; CARBOMER INTERPOLYMER TYPE A (ALLYL SUCROSE CROSSLINKED); TROLAMINE

Tendersant Hand Sanitizer

Active ingredient

Ethyl Alcohol 70%

Purpose

Antiseptic

Uses:

To decrease bacteria on the skin.

Recommended for repeated use.

Warnings

Keep away from fire or flame. Flammable.

Avoid contact with broken skin. For external use only.

When using this product

do not use in or near the eyes. In case of contact, rinse eyes thoroughly with water

Stop use:

if irritation or redness develops.

- If condition persists for more than 72 hours consult a doctor.

Keep out of reach of children

If swallowed, get medical help

Directions:

Not recommended for infants

- Wet hands thoroughly with product and allow to dry without wiping
- Children under 6 years of age should be supervised when using this product.

Other information:

Do not store above 110°F,

May discolor some fabrics..

Inactive ingredients:

Water, Aloe Barbadensis Leaf Juice, Maltodextrin, Glycerin, Propylene Glycol, Acrylates/C10-30 Alkyl Acrylate crosspolymer, Triethanolamine, Fragrance.